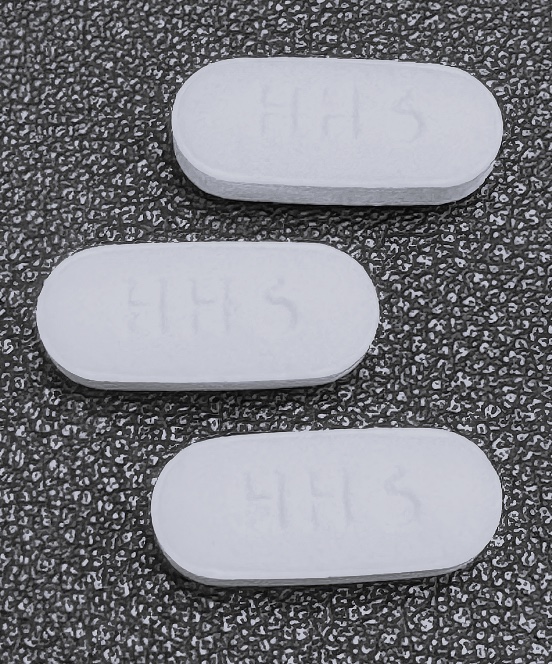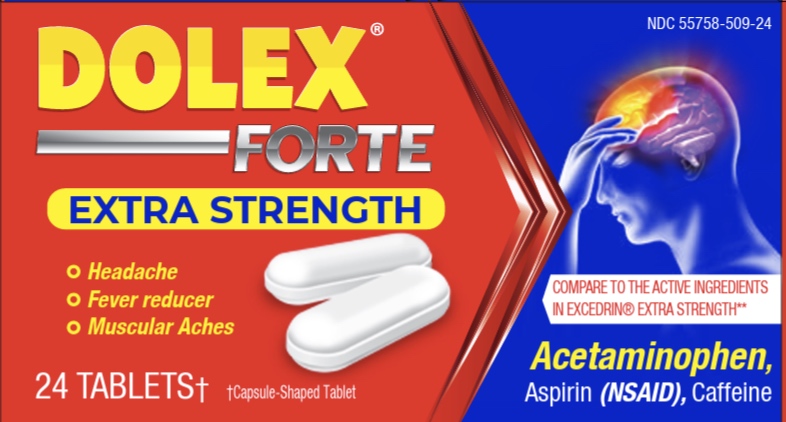 DRUG LABEL: Dolex Forte
NDC: 55758-509 | Form: TABLET
Manufacturer: Pharmadel LLC
Category: otc | Type: HUMAN OTC DRUG LABEL
Date: 20251217

ACTIVE INGREDIENTS: ACETAMINOPHEN 250 mg/1 1; ASPIRIN 250 mg/1 1; CAFFEINE 65 mg/1 1
INACTIVE INGREDIENTS: POLYETHYLENE GLYCOL 400; TALC; STARCH, CORN; SILICON DIOXIDE; POVIDONE K30; HYPROMELLOSE, UNSPECIFIED; CELLULOSE, MICROCRYSTALLINE; STEARIC ACID; WATER

Dolex Forte (HHH Pharma)

Active ingredients and Purposes

.

PURPOSE

Active ingredients | Purposes
Acetaminophen 250 mg................... | Pain reliever
Aspirin 250 mg (NSAID*)................ | Pain reliever
Caffeine 65 mg................................. | Pain reliever aid

* nonsteroidal anti-inflammatory drug

Drug Facts

.

Uses

Temporarily relieves minor aches and pains due to:

- headache
- a cold
- arthritis
- muscular aches
- toothache
- premenstrual and menstrual cramps and bloating

Warnings

Reye’s syndrome:Children and teenagers who have or are recovering from chicken pox or flu-like symptoms should not use this product. When using this product, if changes in behavior with nausea and vomiting occur, consult a doctor because these symptoms could be an early sign of Reye's syndrome, a rare but serious illness.

Allergy alert: Acetaminophen may cause severe skin reactions. Symptoms may include:

- skin reddening
- blisters
- rash. If a skin reaction occurs, stop use and seek medical help right away.

Allergy alert: Aspirin (NSAID) may cause severe allergic reactions. Symptoms may include:

- hives
- facial swelling
- asthma (wheezing)
- shock

Liver warning:This product contains Acetaminophen. Severe liver damage may occur if you take

- more than 8 tabletsin 24 hours, which is the maximum daily amount
- with other drugs containing acetaminophen
- 3 or more alcoholic drinks everyday while using this product

Stomach bleeding warning:This product contains a nonsteroidal anti-inflammatory drug (NSAID), which may cause severe stomach bleeding. The chance is higher if you:

- are age 60 or older
- have had stomach ulcers or bleeding problems
- take a blood thinning (anticoagulant) or steroid drug
- take other drugs containing prescription or nonprescription NSAIDs (aspirin, ibuprofen, naproxen, or others)
- have 3 or more alcoholic drinks everyday while using this product
- take more or for a longer time than directed

Caffeine warning:The recommended dose of this product contains about as much caffeine as a cup of coffee. Limit the use of caffeine-containing medications, foods, or beverages while taking this product because too much caffeine may cause nervousness, irritability, sleeplessness, and occasionally a rapid heartbeat.

Do not use

- if you have ever had an allergic reaction to acetaminophen, aspirin or any other pain reliever/fever reducer
- with any other drug containing acetaminophen(prescription or nonprescription). If you are not sure whether a drug contains acetaminophen, ask a doctor or pharmacist.

Ask a doctor before use if

- you have liver disease
- you have asthma
- stomach bleeding warning applies to you
- you have a history of stomach problems, such as heartburn
- you have high blood pressure, heart disease, liver cirrhosis, or kidney disease
- you are taking a diuretic

Ask a doctor or pharmacist before use if you are taking

- a prescription drug for diabetes, gout, or arthritis
- any other drug, or are under a doctor's care for any serious condition

Stop use and ask a doctor if

- an allergic reaction occurs. Seek medical help right away.
- you experience any of the following signs of stomach bleeding:
- feel faint
- vomit blood
- have bloody or black stools
- have stomach pain that does not get better
- ringing in the ears or loss of hearing occurs
- redness or swelling is present
- pain gets worse or lasts for more than 10 days
- fever gets worse or lasts for more than 3 days
- any new symptoms appear.

These could be signs of a serious condition.

If pregnant or breastfeeding,

ask a health professional before use. It is especially important not to use aspirin during the last 3 months of pregnancy unless definitely directed to do so by a doctor because it may cause problems in the unborn child or complications during delivery.

Keep out of reach of children.

In case of overdose, get medical help or contact a Poison Control Center right away (1-800-222-1222). Prompt medical attention is critical for adults as well as for children even if you do not notice any signs or symptoms.

Directions

- do not take more than directed (See WARNINGS)
- adults and children 12 years of age and older:take two (2) tablets every 6 hours with a full glass of water. Do not take more than 8 tablets in 24 hours. children under 12 years of age:consult a doctor

Other information

- store between 68-77˚F (20-25˚C)
- keep box for important information
- read all product information before use

Inactive ingredients

corn starch, hypromellose, microcrystalline cellulose, polyethylene glycol 400, povidone k30, silicon dioxide, stearic acid, talc, water

Dist. by/ por:

Pharmadel LLC

New Castle, DE 19720

Questions? +1-866-359-3478

**This product is not manufactured or distributed by GSK Consumer Healthcare, distributor of Excedrin® Extra Strength